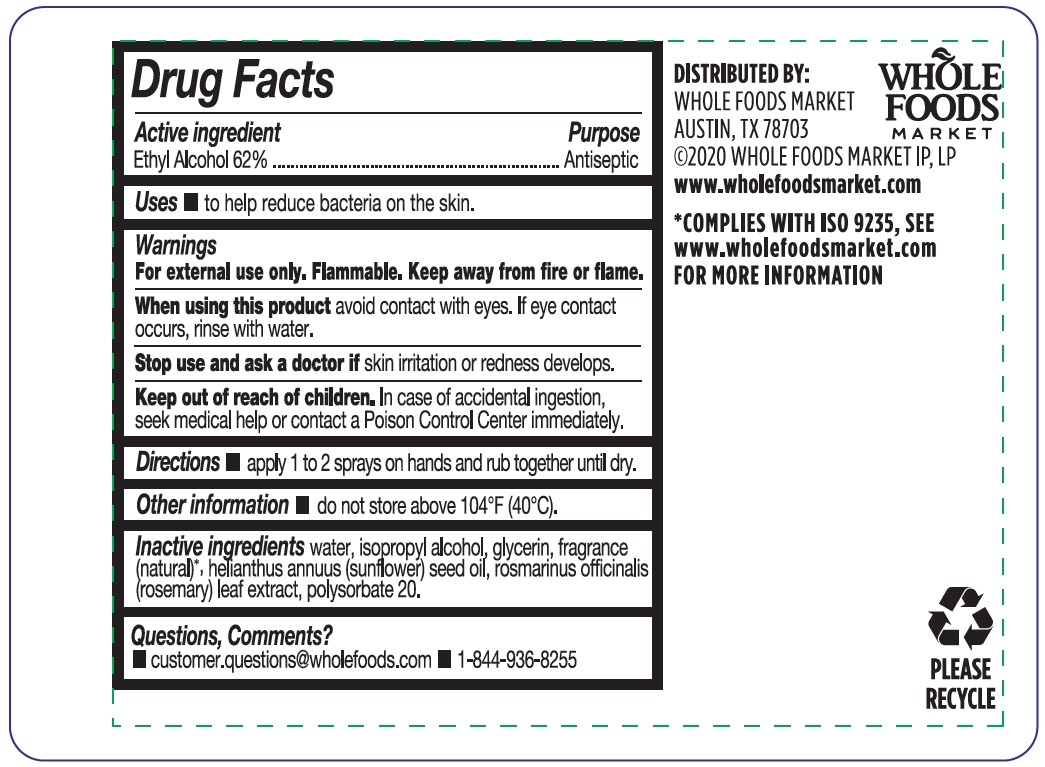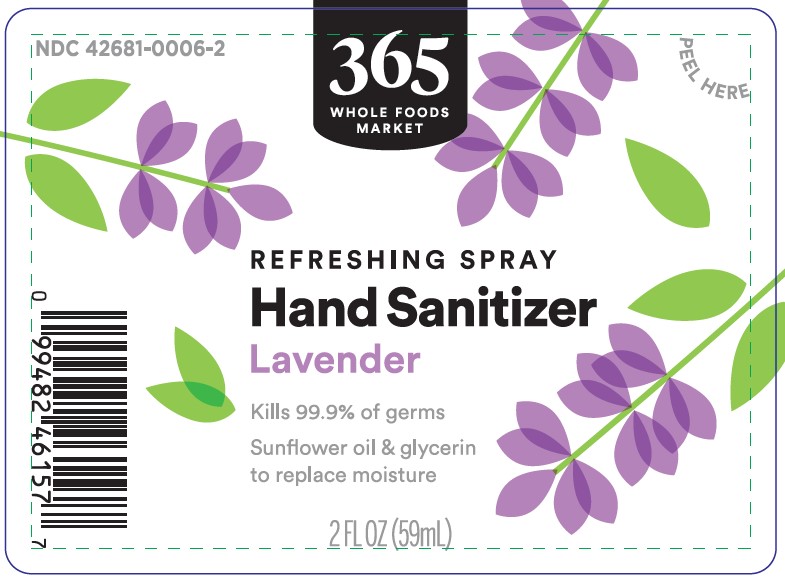 DRUG LABEL: Hand Sanitizer
NDC: 42681-0006 | Form: SPRAY
Manufacturer: Whole Foods Market, Inc.
Category: otc | Type: HUMAN OTC DRUG LABEL
Date: 20241102

ACTIVE INGREDIENTS: ALCOHOL 62 mL/100 mL
INACTIVE INGREDIENTS: ISOPROPYL ALCOHOL; WATER; GLYCERIN; SUNFLOWER OIL; ROSEMARY; POLYSORBATE 20

Whole Foods 365 Hand Sanitizer Spray - Lavender 2 fl oz

Active ingredient Purpose
Ethyl Alcohol 62% Antiseptic

PURPOSE

Uses ■ to help reduce bacteria on the skin.

WARNINGS

For external use only. Flammable. Keep away from fire or flame.

When using this product avoid contact with eyes. If eye contact occurs, rinse with water.

Stop use and ask a doctor if skin irritation or redness develops.

Keep out of reach of children. In case of accidental ingestion, seek medical help or contact a Poison Control Center immediately.

DOSAGE AND ADMINISTRATION

Directions ■ apply 1 to 2 sprays on hands and rub together until dry

Other information ■ do not store above 104°F (40°C).

INACTIVE INGREDIENT

Inactive ingredients water, isopropyl alcohol, glycerin, fragrance (natural)*, helianthus annuus (sunflower) seed oil, rosmarinus
officinalis (rosemary) leaf extract, polysorbate 20.

*Complies within ISO 9235, see www.wholefoodsmarket.com for more information

QUESTIONS

Questions, Comments? ■ customer.questions@wholefoods.com ■ 1-844-936-8255